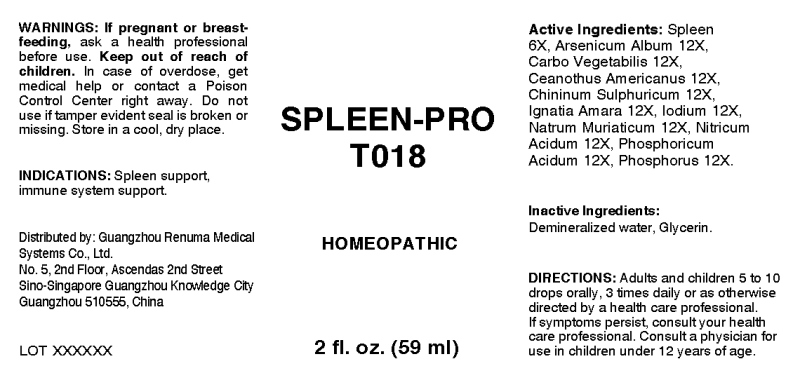 DRUG LABEL: Spleen-Pro
NDC: 71742-0012 | Form: LIQUID
Manufacturer: Guangzhou Renuma Medical Systems Co., Ltd
Category: homeopathic | Type: HUMAN OTC DRUG LABEL
Date: 20171026

ACTIVE INGREDIENTS: SUS SCROFA SPLEEN 6 [hp_X]/1 mL; ARSENIC TRIOXIDE 12 [hp_X]/1 mL; ACTIVATED CHARCOAL 12 [hp_X]/1 mL; CEANOTHUS AMERICANUS LEAF 12 [hp_X]/1 mL; QUININE SULFATE 12 [hp_X]/1 mL; STRYCHNOS IGNATII SEED 12 [hp_X]/1 mL; IODINE 12 [hp_X]/1 mL; SODIUM CHLORIDE 12 [hp_X]/1 mL; NITRIC ACID 12 [hp_X]/1 mL; PHOSPHORIC ACID 12 [hp_X]/1 mL; PHOSPHORUS 12 [hp_X]/1 mL
INACTIVE INGREDIENTS: WATER; GLYCERIN

Drug Facts:

ACTIVE INGREDIENTS:

Spleen (Suis) 6X, Arsenicum Album 12X, Carbo Vegetabilis 12X, Ceanothus Americanus 12X, Chininum Sulphuricum 12X, Ignatia Amara 12X, Iodium 12X, Natrum Muriaticum 12X, Nitricum Acidum 12X, Phosphoricum Acidum 12X, Phosphorus 12X.Spleen (Suis) 6X, Arsenicum Album 12X, Carbo Vegetabilis 12X, Ceanothus Americanus 12X, Chininum Sulphuricum 12X, Ignatia Amara 12X, Iodium 12X, Natrum Muriaticum 12X, Nitricum Acidum 12X, Phosphoricum Acidum 12X, Phosphorus 12X.

INDICATIONS:

Spleen support, immune system support.

WARNINGS:

If pregnant or breast-feeding, ask a health professional before use.
Keep out of reach of children. In case of overdose, get medical help or contact a Poison Control Center right away.
Do not use if tamper evident seal is broken or missing. Store in a cool, dry place.

Keep out of reach of children. In case of overdose, get medical help or contact a Poison Control Center right away.

DIRECTIONS:

Adults and children 5 to 10 drops orally, 3 times daily or as otherwise directed by a health care professional. If symptoms persist, consult your health care professional.
Consult a physician for use in children under 12 years of age.

INDICATIONS:

Spleen support, immune system support.

INACTIVE INGREDIENTS:

Demineralized water, Glycerin

QUESTIONS:

Distributed by:
Guangzhou Renuma Medical
Systems Co., Ltd.
No. 5, 2nd Floor, Ascendas 2nd Street
Sino-Singapore Guangzhou Knowledge City
Guangzhou 510555, China

PACKAGE LABEL DISPLAY:

SPLEEN-PRO
T018
HOMEOPATHIC
2 fl. oz. (59 ml)